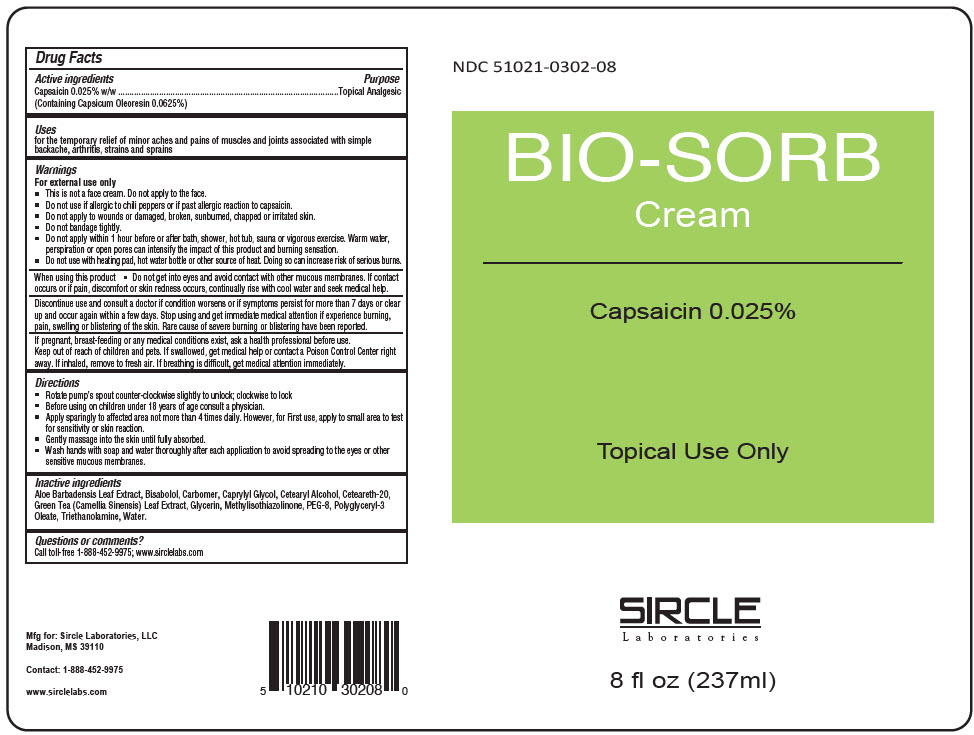 DRUG LABEL: Bio-Sorb
NDC: 51021-302 | Form: CREAM
Manufacturer: Sircle Laboratories, LLC
Category: otc | Type: HUMAN OTC DRUG LABEL
Date: 20210712

ACTIVE INGREDIENTS: CAPSAICIN 0.025 mg/1 mL
INACTIVE INGREDIENTS: WATER; CETOSTEARYL ALCOHOL; POLYOXYL 20 CETOSTEARYL ETHER; ALOE VERA LEAF; GREEN TEA LEAF; LEVOMENOL; POLYETHYLENE GLYCOL 800; CARBOMER HOMOPOLYMER, UNSPECIFIED TYPE; POLYGLYCERYL-3 OLEATE; CAPRYLYL GLYCOL; METHYLISOTHIAZOLINONE; GLYCERIN; TROLAMINE

Bio-Sorb

Drug Facts

Active ingredients

Capsaicin 0.025% w/w (Containing Capsicum Oleoresin 0.0625%)

Purpose

Topical Analgesic

Uses

for the temporary relief of minor aches and pains of muscles and joints associated with simple backache, arthritis, strains and sprains

Warnings

For external use only

- This is not a face cream. Do not apply to the face.
- Do not use if allergic to chili peppers or if past allergic reaction to capsaicin.
- Do not apply to wounds or damaged, broken, sunburned, chapped or irritated skin.
- Do not bandage tightly.
- Do not apply within 1 hour before or after bath, shower, hot tub, sauna or vigorous exercise. Warm water, perspiration or open pores can intensify the impact of this product and burning sensation.
- Do not use with heating pad, hot water bottle or other source of heat. Doing so can increase risk of serious burns.

When using this product

- Do not get into eyes and avoid contact with other mucous membranes. If contact occurs or if pain, discomfort or skin redness occurs, continually rise with cool water and seek medical help.

STOP USE

Discontinue use and consult a doctor if condition worsens or if symptoms persist for more than 7 days or clear up and occur again within a few days. Stop using and get immediate medical attention if experience burning, pain, swelling or blistering of the skin. Rare cause of severe burning or blistering have been reported.

PREGNANCY OR BREAST FEEDING

If pregnant, breast-feeding or any medical conditions exist, ask a health professional before use.

Keep out of reach of children and pets. If swallowed, get medical help or contact a Poison Control Center right away. If inhaled, remove to fresh air. If breathing is difficult, get medical attention immediately.

Directions

- Rotate pump's spout counter-clockwise slightly to unlock; clockwise to lock
- Before using on children under 18 years of age consult a physician.
- Apply sparingly to affected area not more than 4 times daily. However, for First use, apply to small area to test for sensitivity or skin reaction.
- Gently massage into the skin until fully absorbed.
- Wash hands with soap and water thoroughly after each application to avoid spreading to the eyes or other sensitive mucous membranes.

Inactive ingredients

Aloe Barbadensis Leaf Extract, Bisabolol, Carbomer, Caprylyl Glycol, Cetearyl Alcohol, Ceteareth-20, Green Tea (Camellia Sinensis) Leaf Extract, Glycerin, Methylisothiazolinone, PEG-8, Polyglyceryl-3 Oleate, Triethanolamine, Water.

Questions or comments?

Call toll-free 1-888-452-9975; www.sirclelabs.com

PRINCIPAL DISPLAY PANEL - 237 ml Bottle Label

NDC 51021-0302-08

BIO-SORB
Cream

Capsaicin 0.025%

Topical Use Only

SIRCLE
Laboratories

8 fl oz (237ml)